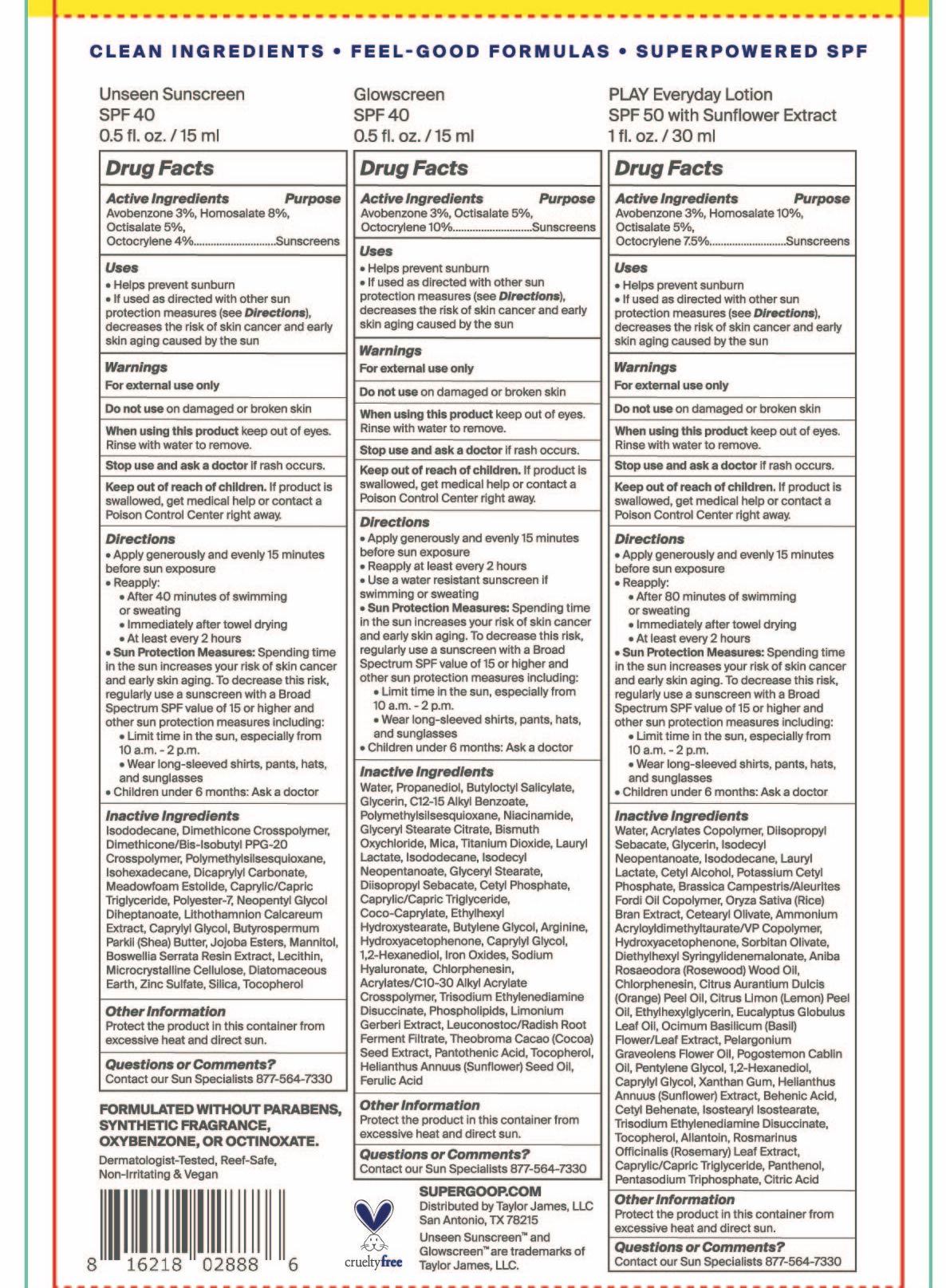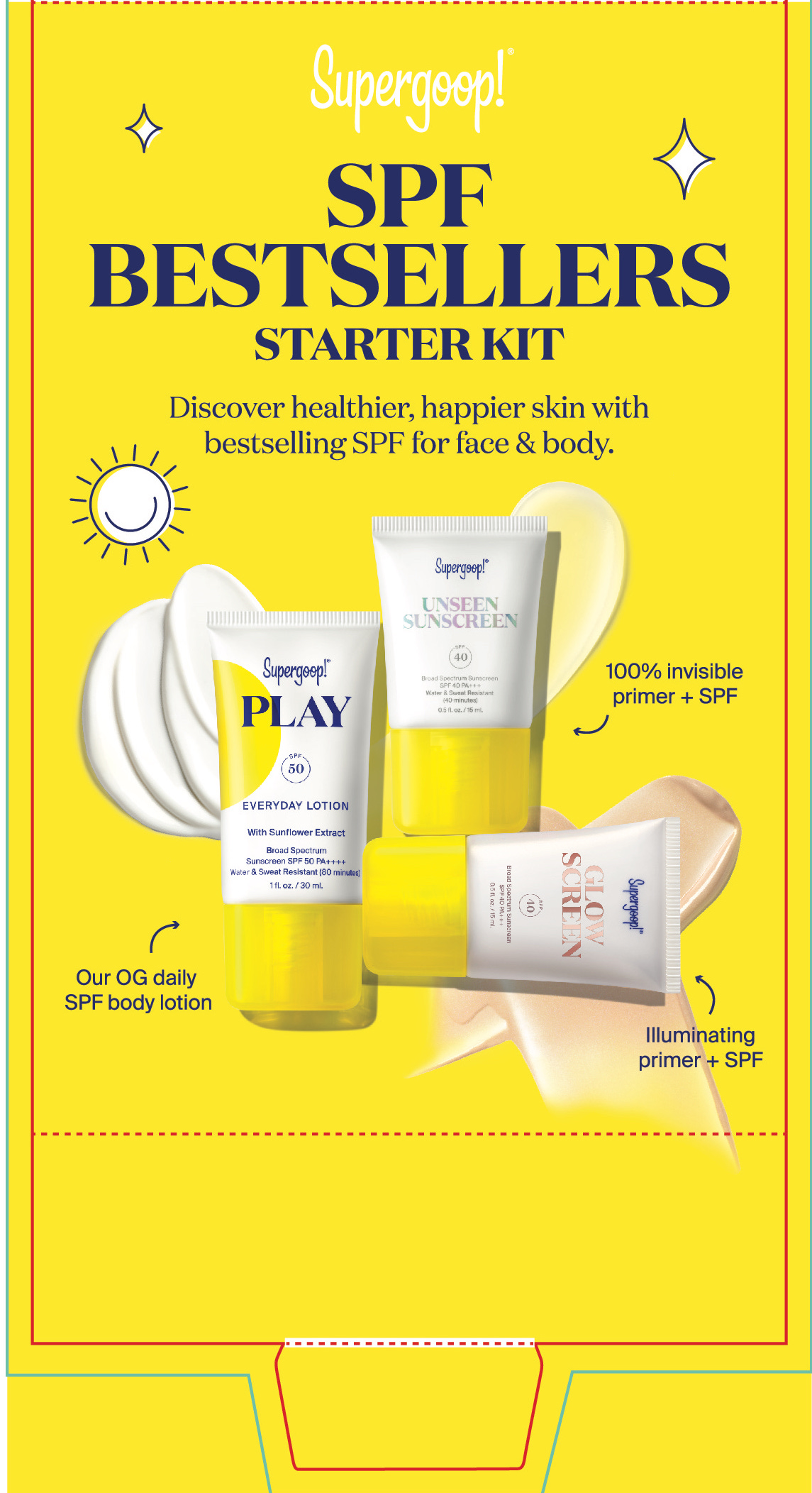 DRUG LABEL: SPF Bestsellers Starter Kit
NDC: 75936-410 | Form: KIT | Route: TOPICAL
Manufacturer: Supergoop, LLC
Category: otc | Type: HUMAN OTC DRUG LABEL
Date: 20230711

ACTIVE INGREDIENTS: AVOBENZONE 3 g/100 mL; OCTISALATE 5 g/100 mL; OCTOCRYLENE 10 g/100 mL; HOMOSALATE 8 g/100 mL; AVOBENZONE 3 g/100 mL; OCTOCRYLENE 4 g/100 mL; OCTISALATE 5 g/100 mL; HOMOSALATE 10 g/100 mL; OCTISALATE 5 g/100 mL; OCTOCRYLENE 7.5 g/100 mL; AVOBENZONE 3 g/100 mL
INACTIVE INGREDIENTS: NIACINAMIDE; ETHYLHEXYL HYDROXYSTEARATE; BUTYLENE GLYCOL; HYDROXYACETOPHENONE; CAPRYLYL GLYCOL; MEDIUM-CHAIN TRIGLYCERIDES; LIMONIUM GERBERI WHOLE; LEUCONOSTOC/RADISH ROOT FERMENT FILTRATE; PANTOTHENIC ACID; TOCOPHEROL; SUNFLOWER OIL; ISODODECANE; ARGININE; CETYL PHOSPHATE; COCO-CAPRYLATE; 1,2-HEXANEDIOL; WATER; BUTYLOCTYL SALICYLATE; ISODECYL NEOPENTANOATE; GLYCERYL MONOSTEARATE; COCOA; PROPANEDIOL; ALKYL (C12-15) BENZOATE; POLYMETHYLSILSESQUIOXANE (4.5 MICRONS); FERULIC ACID; DIISOPROPYL SEBACATE; TRISODIUM ETHYLENEDIAMINE DISUCCINATE; GLYCERIN; GLYCERYL STEARATE CITRATE; BISMUTH OXYCHLORIDE; MICA; TITANIUM DIOXIDE; LAURYL LACTATE; CHLORPHENESIN; HYALURONATE SODIUM; FERRIC OXIDE RED; CARBOMER INTERPOLYMER TYPE A (ALLYL SUCROSE CROSSLINKED); POLYESTER-7; NEOPENTYL GLYCOL DIHEPTANOATE; ZINC SULFATE; TOCOPHEROL; PHYMATOLITHON CALCAREUM; SHEA BUTTER; INDIAN FRANKINCENSE; DIATOMACEOUS EARTH; DICAPRYLYL CARBONATE; MEDIUM-CHAIN TRIGLYCERIDES; MANNITOL; POLYMETHYLSILSESQUIOXANE (11 MICRONS); ISOHEXADECANE; MICROCRYSTALLINE CELLULOSE; SILICON DIOXIDE; LECITHIN, SUNFLOWER; DIMETHICONE CROSSPOLYMER (450000 MPA.S AT 12% IN CYCLOPENTASILOXANE); DIMETHICONE/BIS-ISOBUTYL PPG-20 CROSSPOLYMER; ISODODECANE; ISODODECANE; WATER; DIISOPROPYL SEBACATE; GLYCERIN; ISODECYL NEOPENTANOATE; LAURYL LACTATE

SPF Bestsellers Starter Kit

Unseen Sunscreen Active Ingredient

Active Ingredients Purpose

Avobenzone 3% Sunscreen

Homosalate 8% Sunscreen

Octocrylene 4% Sunscreen

Octisalate 5% Sunscreen

Glowscreen SPF 40

Active Ingredients Purpose
Avobenzone 3% Sunscreen
Octisalate 5% Sunscreen
Octocylene 10% Sunscreen

Play Everyday Sunscreen SPF 50 with Sunflower Extract Active ingredients

Active Ingredients Purpose

Avobenzone 3% Sunscreen

Homosalate 10% Sunscreen

Octisalate 5% Sunscreen

Octocrylene 7.5% Sunscreen

Uses

Helps Prevent Sunburn

If used as directed with other sun protection measures (see Directions), decreases the risk of Skin cancer and early skin aging caused by the sun

Keep out of reach of children. If product is swallowed, get medical help or contact a Poison Control Center right away

Stop use and ask a doctor if rash occurs.

WARNINGS

For External use only

Do not use on damaged or broken skin

When using this product, Keep out of eyes. Rinse with water to remove

Unseen Sunscreen SPF 40 Directions

Directions

- apply generously and evenly 15 minutes before sun exposure
- reapply:

after 40 minutes of swimming or sweating

immediately after towel drying

at least every 2 hours

- Sun Protection Measures Spending time in the sun increases your risk of skin cancer and early skin aging. To decrease this risk, regularly use a sunscreen with a Broad Spectrum SPF value of 15 or higher and other sun protection measures including:
- Limit time in the sun, especially from 10 a.m.-2 p.m.
- Wear long-sleeved shirts, pants, hats, and sunglasses
- Children under 6 months: ask a doctor

Glowscreen SPF 40 Directions

Directions

- Apply generously and evenly 15 minutes before sun exposure
- Reapply at least every 2 hours

Use a water resistant sunscreen if swimming or sweating
Sun Protection Measures: Spending time in the sun increases your risk of skin cancer and early skin aging. To decrease this risk, regularly use a sunscreen with a Broad Spectrum SPF value of 15 or higher and other sun protection measures including:
Limit time in the sun, especially from 10a.m. – 2p.m.

- Wear long-sleeved shirts, pants, hats, and sunglasses
- Children under 6 months: Ask a doctor

Play Everyday Sunscreen SPF 50 with Sunflower Extract directions

Directions

- Apply liberally 15 minutes before sun exposure

Reapply:

- after 80 minutes of swimming or sweating
- immediately after towel drying
- at least every 2 hours
- Sun Protection Measures. Spending time in the sun increases your risk of skin

cancer and early skin aging. To decrease this risk, regularly use a sunscreen
with broad spectrum SPF of 15 or higher and other sun protection measures
including:

- limit time in the sun, especially from 10 a.m. - 2 p.m.
- Wear Long-sleeved shirts, pants, hats, and sunglasses
- Children under 6 months: Ask a doctor

Unseen Sunscreen Inactive Ingredients

Inactive Ingredients

Isododecane, Dimethicone Crosspolymer, Dimethicone/Bis-Isobutyl PPG-20 Crosspolymer, Polymethylsilsesquioxane, Isohexadecane, Dicrapylyl Carbonate, Meadowfoam Estolide, Caprylic/Capric Triglyceride, Polyester-7, Neopentyl Glycol Diheptanoate, Lithothamnion Calcareum Extract,Butyrospermum Parkii (Shea) Butter, Jojoba Esters, Mannitol, Boswellia Serrata Resin Extract, Lecithin, Microcrystalline Cellulose, Diatomaceous Earth, Zinc Sulfate, Silica, Tocopherol

Glowscreen SPF 40 inactive ingredients

Inactive Ingredients
Water, Propanediol, Butyloctyl Salicylate, Glycerin, C12-15 Alkyl Benzoate, Polymethylsilsesquioxane, Niacinamide, Glyceryl Stearate Citrate, Bismuth Oxychloride, Mica, Titanium Dioxide, Lauryl Lactate, Isododecane, Isodecyl Neopentanoate, Glyceryl Stearate, Diisopropyl Sebacate, Cetyl Phosphate, Caprylic/Capric Triglyceride, Coco-Caprylate, Ethylhexyl Hydroxystearate, Butylene Glycol, Arginine, Hydroxyacetophenone, Caprylyl Glycol, 1,2-Hexanediol, Iron Oxides, Sodium Hyaluronate, Chlorphenesin, Acrylates/C10-30 Alkyl Acrylate Crosspolymer, Trisodium Ethylenediamine Disuccinate, Phospholipids, Limonium Gerberi Extract, Leuconostoc/Radish Root Ferment Filtrate, Theobroma Cacao (Cocoa) Seed Extract, Pantothenic Acid, Tocopherol, Helianthus Annuus (sunflower) Seed Oil, Ferulic Acid

Play Everyday Lotion SPF 50 with Sunflower extract

Inactive Ingredients

Water, Acrylates Copolymer, Diisopropyl Sebacate, Glycerin, Isodecyl Neopentanoate, Isododecane, Lauryl Lactate, Cetyl Alcohol, Potassium Cetyl Phosphate, Brassica Camprestris/Aleurites Fordi Copolymer, Oryza Sativa (Rice) Bran Extract, Cetearyl Olivate, Ammonium Acryloyldimethyltaurate/VP Copolymer, Hydroxyacetophenone, Sorbitan Olivate, Diethylhexyl Syringylidenemalonate, Aniba Rosaeodora (Rosewood) Wood Oil, Chlorphenesin, Citrus Aurantium Dulcis (Orange) Peel Oil, Citrus Limon (Lemon) Peel Oil, Ethylhexylglycerin, Eucalyptus Globulus Leaf Oil, Ocimum Bascilicum (Basil) Flower/Leaf Extract, Pelargonium Graveolens Flower Oil, Pogostemon Cablin Oil, Pentylene Glycol, 1,2-hexanediol, Caprylyl Glycol, Xanthan Gum, Helianthus Annuus (Sunflower) Extract, Behenic Acid, Cetyl Behenate, Isostearyl Isostearate, Trisodium Ethylenediamene Disuccinate, Tocopherol, Allantoin, Rosmarinus Officinalis (Rosemary) Leaf Extract, Caprylic/Capric Triglyceride,Panthenol, Pentasodium Triphosphate, Citric Acid

SPF Bestsellers Starter Kit

Discover healthier, happier skin with bestselling SPF for face & body.

Unseen Sunscreen SPF 40

0.5 fl. oz. / 15 ml

Glowscreen SPF 40

0.5fl. oz. / 15 ml

Play Everyday Lotion SPF 50 with Sunflower Extract

1 fl. oz. / 30 ml